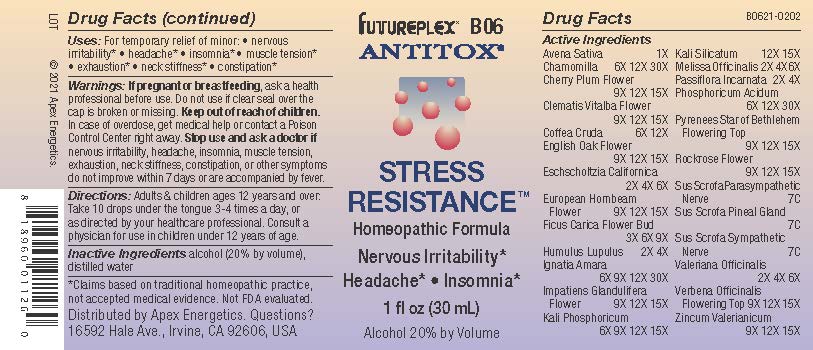 DRUG LABEL: B06
NDC: 63479-0206 | Form: SOLUTION/ DROPS
Manufacturer: Apex Energetics Inc.
Category: homeopathic | Type: HUMAN OTC DRUG LABEL
Date: 20240108

ACTIVE INGREDIENTS: FICUS CARICA FLOWER BUD 9 [hp_X]/1 mL; HOPS 4 [hp_X]/1 mL; IMPATIENS GLANDULIFERA FLOWER 15 [hp_X]/1 mL; ZINC VALERATE DIHYDRATE 15 [hp_X]/1 mL; QUERCUS ROBUR FLOWER 15 [hp_X]/1 mL; PRUNUS CERASIFERA FLOWER 15 [hp_X]/1 mL; ARABICA COFFEE BEAN 12 [hp_X]/1 mL; CLEMATIS VITALBA FLOWER 15 [hp_X]/1 mL; DIBASIC POTASSIUM PHOSPHATE 15 [hp_X]/1 mL; VERBENA OFFICINALIS FLOWERING TOP 15 [hp_X]/1 mL; MELISSA OFFICINALIS 6 [hp_X]/1 mL; MATRICARIA CHAMOMILLA 30 [hp_X]/1 mL; AVENA SATIVA FLOWERING TOP 1 [hp_X]/1 mL; STRYCHNOS IGNATII SEED 30 [hp_X]/1 mL; PHOSPHORIC ACID 30 [hp_X]/1 mL; ORNITHOGALUM UMBELLATUM FLOWERING TOP 15 [hp_X]/1 mL; CARPINUS BETULUS FLOWER 15 [hp_X]/1 mL; SUS SCROFA PINEAL GLAND 7 [hp_C]/1 mL; VALERIAN 6 [hp_X]/1 mL; POTASSIUM SILICATE 15 [hp_X]/1 mL; PASSIFLORA INCARNATA FLOWERING TOP 4 [hp_X]/1 mL; HELIANTHEMUM NUMMULARIUM FLOWER 15 [hp_X]/1 mL; SUS SCROFA PARASYMPATHETIC NERVE 7 [hp_C]/1 mL; SUS SCROFA SYMPATHETIC NERVE 7 [hp_C]/1 mL; ESCHSCHOLZIA CALIFORNICA 6 [hp_X]/1 mL
INACTIVE INGREDIENTS: ALCOHOL; WATER

B06

Active Ingredients
Avena Sativa | 1X
Chamomilla | 6X 12X 30X
Cherry Plum Flower | 9X 12X 15X
Clematis Vitalba Flower | 9X 12X 15X
Coffea Cruda | 6X 12X
English Oak Flower | 9X 12X 15X
Eschscholtzia Californica | 2X 4X 6X
European Hornbeam Flower | 9X 12X 15X
Ficus Carica Flower Bud | 3X 6X 9X
Humulus Lupulus | 2X 4X
Ignatia Amara | 6X 9X 12X 30X
Impatiens Glandulifera Flower | 9X 12X 15X
Kali Phosphoricum | 6X 9X 12X 15X
Kali Silicatum | 12X 15X
Melissa Officinalis | 2X 4X 6X
Passiflora Incarnata | 2X 4X
Phosphoricum Acidum | 6X 12X 30X
Pyrenees Star Of Bethlehem Flowering Top | 9X 12X 15X
Rockrose Flower | 9X 12X 15X
Sus Scrofa Parasympathetic Nerve | 7C
Sus Scrofa Pineal Gland | 7C
Sus Scrofa Sympathetic Nerve | 7C
Valeriana Officinalis | 2X 4X 6X
Verbena Officinalis Flowering Top | 9X 12X 15X
Zincum Valerianicum | 9X 12X 15X

INDICATIONS AND USAGE

Uses:

For temporary relief of minor:

nervous irritability*

headache*

insomnia*

muscle tension*

exhaustion*

neck stiffness*

constipation*

Warnings:

PREGNANCY OR BREAST FEEDING

If pregnant or breastfeeding, ask a health professional before use.

Do not use if clear seal over the cap is broken or missing.

Keep out of reach of children. In case of overdose, get medical help or contact a Poison Control Center right away.

Stop use and ask a doctor if nervous irritability, headache, insomnia, muscle tension, exhaustion, neck stiffness, constipation, or other symptoms do not improve within 7 days or are accompanied by fever.

Directions:

Adults & children ages 12 years and over: Take 10 drops under the tongue 3-4 times a day, or as directed by your healthcare professional. Consult a physician for use in children under 12 years of age.

Inactive Ingredients

alcohol (20% by volume), distilled water

Distributed by Apex Energetics. Questions?

16592 Hale Ave., Irvine, CA 92606, USA

PACKAGE LABEL

FUTUREPLEX® B06

ANTITOX®

STRESS RESISTANCE™

Homeopathic Formula

Nervous Irritability*

Headache*

Insomnia*

1 fl oz (30 mL)

Alcohol 20% by Volume